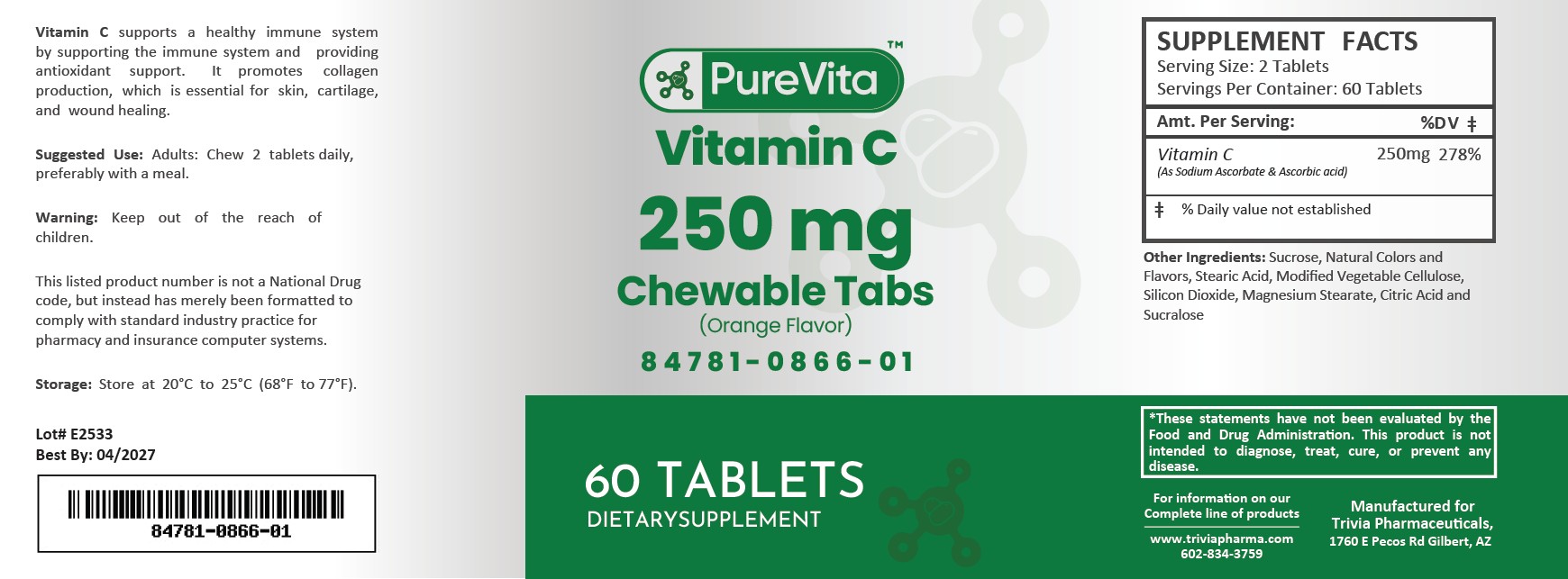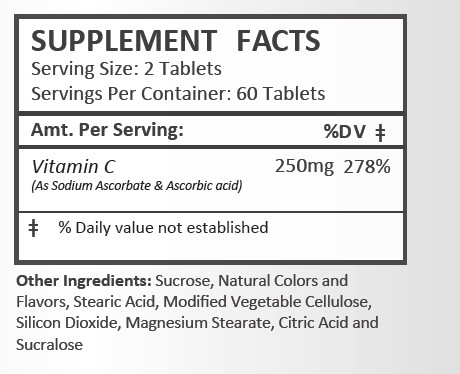 DRUG LABEL: Vitamin C
NDC: 84781-866 | Form: TABLET, CHEWABLE
Manufacturer: Trivia Pharmaceuticals, LLC
Category: other | Type: Dietary Supplement
Date: 20250616

ACTIVE INGREDIENTS: ASCORBIC ACID 400 mg/1 1

Vitamin C 250mg

Health Claim Section:

Vitamin C 250 mg Chewable Tablets

Description:

Vitamin C supports a healthy immune system by supporting the immune system and providing antioxidant support. It promotes collagen production, which is essential for skin, cartilage, and wound healing.

This listed product is not a National Drug Code, but instead has merely been formatted to comply with standard industry practice for pharmacy and insurance computer systems.

Warnings and Precautions:

This product is contraindicated in patients with a known hypersensitivity to any of the ingredients.

Keep out of the reach of children.

Dosage and Administration:

Adults: Chew 2 tablets daily, preferably with a meal.

How Supplied:

Vitamin C 250 mg tablets are supplied as white, round tablets in plastic bottles of 60 ct.

84781-866-01

These statements have not been evaluated by the Food and Drug Administration. This product is not intended to diagnose, treat, cure or prevent any disease.

All prescriptions using this product shall be pursuant to state statutes as applicable. This is not an Orange Book product. There are no implied or explicit claims on therapeutic equivalence.

Manufactured for:
Trivia Pharmaceuticals

Gilbert, AZ

Storage:

Store at room temperature 20° - 25°C (68° - 77°F)